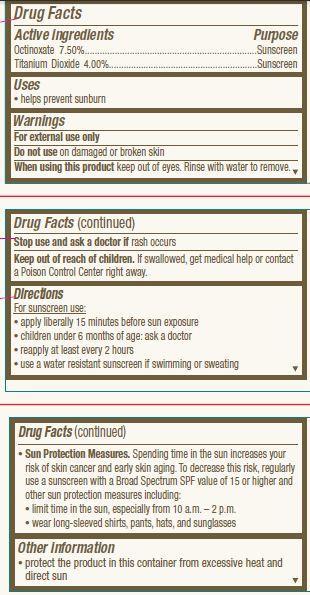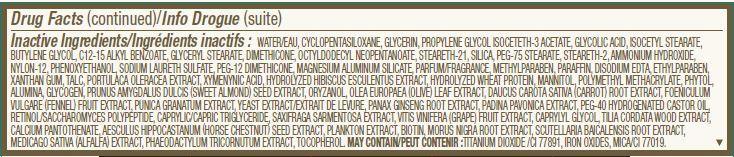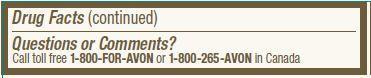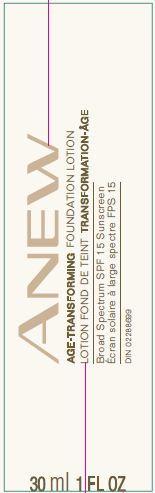 DRUG LABEL: Anew Age-Transforming
NDC: 10096-0324 | Form: LOTION
Manufacturer: New Avon LLC
Category: otc | Type: HUMAN OTC DRUG LABEL
Date: 20160301

ACTIVE INGREDIENTS: OCTINOXATE 75 mg/1 mL; TITANIUM DIOXIDE 40 mg/1 mL

Active ingredients
Octinoxate 7.50%.........................................................................
Titanium Dioxide 4.00%.................................................................

Purpose
..............................Sunscreen
...........................Sunscreen

Uses
• helps prevent sunburn

Warnings
For external use only

Do not use on damaged or broken skin

When using this product keep out of eyes. Rinse with water to remove.

Stop use and ask a doctor if rash occurs

Keep out of reach of children. If swallowed, get medical help or contact a Poison Control Center right away.

Directions

For sunscreen use:
• apply liberally 15 minutes before sun exposure
• children under 6 months of age: ask a doctor
• reapply at least every 2 hours
• use a water resistant sunscreen if swimming or sweating
• Sun Protection Measures. Spending time in the sun increases your risk of skin
cancer and early skin aging. To decrease this risk, regularly use a sunscreen
with a Broad Spectrum SPF value of 15 or higher and other sun protection
measures including:
• limit time in the sun, especially from 10 a.m. – 2 p.m.

• wear long-sleeved shirts, pants, hats, and sunglasses

Other information
• protect the product in this container from excessive heat and direct sun

INACTIVE INGREDIENT

Inactive Ingredients:WATER/EAU, CYCLOPENTASILOXANE, GLYCERIN, PROPYLENE GLYCOL ISOCETETH-3 ACETATE, GLYCOLIC ACID, ISOCETYL STEARATE, BUTYLENE GLYCOL, C12-15 ALKYL BENZOATE, GLYCERYL STEARATE, DIMETHICONE, OCTYLDODECYL NEOPENTANOATE, STEARETH-21, SILICA, PEG-75 STEARATE, STEARETH-2, AMMONIUM HYDROXIDE, NYLON-12, PHENOXYETHANOL, SODIUM LAURETH SULFATE, PEG-12 DIMETHICONE, MAGNESIUM ALUMINUM SILICATE, PARFUM/FRAGRANCE, METHYLPARABEN, PARAFFIN, DISODIUM EDTA, ETHYLPARABEN, XANTHAN GUM, TALC, PORTULACA OLERACEA EXTRACT, XYMENYNIC ACID, HYDROLYZED HIBISCUS ESCULENTUS EXTRACT, HYDROLYZED WHEAT PROTEIN, MANNITOL, POLYMETHYL METHACRYLATE, PHYTOL, ALUMINA, GLYCOGEN, PRUNUS AMYGDALUS DULCIS (SWEET ALMOND) SEED EXTRACT, ORYZANOL, OLEA EUROPAEA (OLIVE) LEAF EXTRACT, DAUCUS CAROTA SATIVA (CARROT) ROOT EXTRACT, FOENICULUM VULGARE (FENNEL) FRUIT EXTRACT, PUNICA GRANATUM EXTRACT, YEAST EXTRACT/EXTRAIT DE LEVURE, PANAX GINSENG ROOT EXTRACT, PADINA PAVONICA EXTRACT, PEG-40 HYDROGENATED CASTOR OIL, RETINOL/SACCHAROMYCES POLYPEPTIDE, CAPRYLIC/CAPRIC TRIGLYCERIDE, SAXIFRAGA SARMENTOSA EXTRACT, VITIS VINIFERA (GRAPE) FRUIT EXTRACT, CAPRYLYL GLYCOL, TILIA CORDATA WOOD EXTRACT, CALCIUM PANTOTHENATE, AESCULUS HIPPOCASTANUM (HORSE CHESTNUT) SEED EXTRACT, PLANKTON EXTRACT, BIOTIN, MORUS NIGRA ROOT EXTRACT, SCUTELLARIA BAICALENSIS ROOT EXTRACT, MEDICAGO SATIVA (ALFALFA) EXTRACT, PHAEODACTYLUM TRICORNUTUM EXTRACT, TOCOPHEROL. MAY CONTAIN:TITANIUM DIOXIDE /CI 77891, IRON OXIDES, MICA/CI 77019.

Questions or Comments?
Call toll free 1-800-FOR-AVON or 1-800-265-AVON in Canada